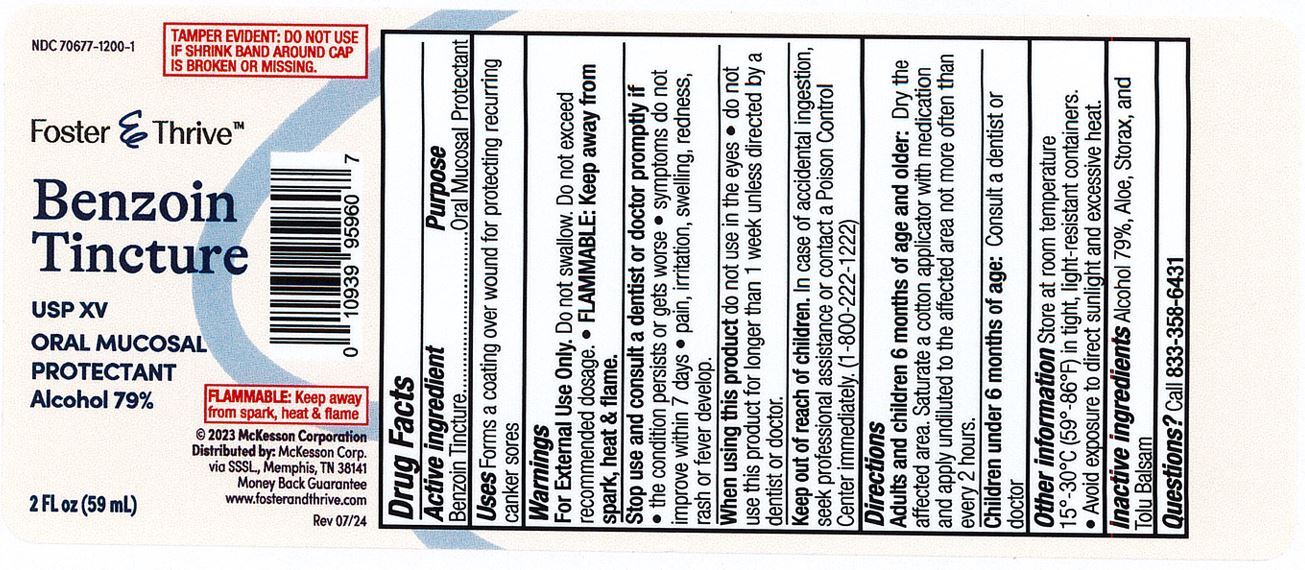 DRUG LABEL: Benzoin Tincture
NDC: 70677-1200 | Form: LIQUID
Manufacturer: 116956644
Category: otc | Type: HUMAN OTC DRUG LABEL
Date: 20241217

ACTIVE INGREDIENTS: BENZOIN RESIN 1000 mg/1 mL
INACTIVE INGREDIENTS: ALCOHOL; ALOE; TOLU BALSAM

Foster & Thrive Benzoin Tincture

Drug Facts

Active Ingredient

Benzoin Tincture

Purpose

Oral mucosal protectant

Use

Forms a coating over wound for protecting recurring canker sores

Warnings

For externl use only. Do not swallow. Do not exceed recommended dosage.

When using this product

do not use in the eyes

do not use this product for longer than 1 week unless directed by a dentist or doctor

Stop use and consult a dentist or doctor if

- the condition persists or gets worse
- symptoms do not improve in 7 days.
- pain, irritation, swelling, redness, rash or fever develop

Keep out of the reach of children.

In case of accidental ingestion, seek professional assistance or contact a Poison Control Center immeditely. (1-800-222-1222)

Directions

Adult and children 6 months of age and older: Dry the affected area. Saturate a cotton applicator with medication and apply undiluted to the affected area not more than every 2 hours.

Children under 6 months of age: Consult a dentist or doctor.

Inactive Ingredients

Alcohol 79%, Aloe, Stoax, Tolu Balsam.

Questions?

Call 833-358-6431